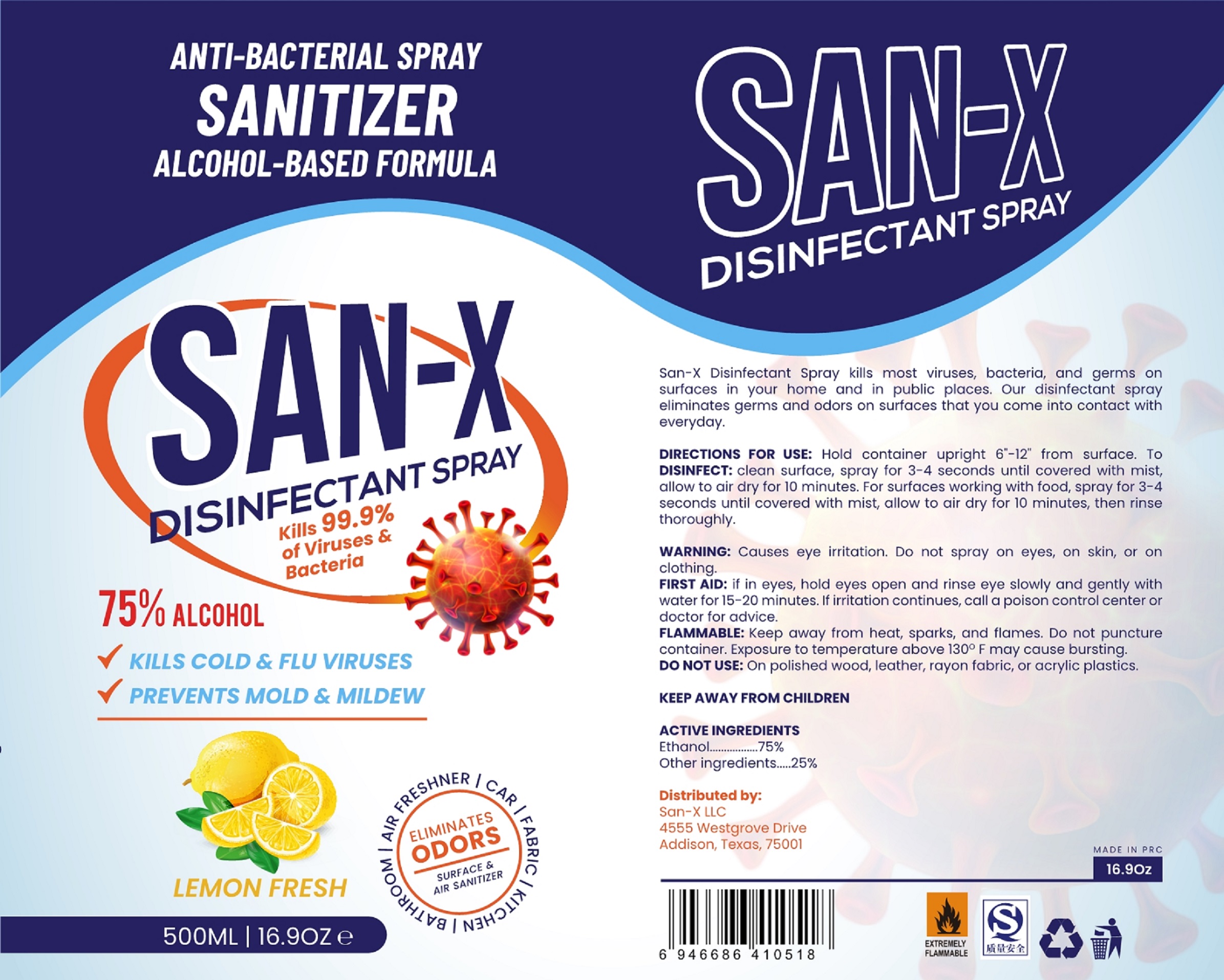 DRUG LABEL: DISINFECTANTSPRAY
NDC: 81276-509 | Form: SPRAY
Manufacturer: Dongyang Medical & Hygienic Articles Co., Ltd.
Category: otc | Type: HUMAN OTC DRUG LABEL
Date: 20201216

ACTIVE INGREDIENTS: ALCOHOL 375 mL/500 mL
INACTIVE INGREDIENTS: LEMON; WATER

81276-509 DISINFECTANT SPRAY LEMON 20200925

Active Ingredient(s)

Alcohol 75% v/v. Purpose: DISINFECTANT

Purpose

DISINFECTANT

Use

Hold container upright 6"-12" from surface. To clean surface, spray for 3-4 seconds until covered with mist, allow to air dry for 10 minutes. For surfaces working with food, spray for 3-4 seconds until covered with mist, allow to air dry for 10 minutes, then rinse thoroughly.

Warnings

- Causes eye irritation. Do not spray on eyes, on skin, or on clothing.
- Keep away from heat, sparks, and flames. Do not puncture container. Exposure to temperature above 130℉ may cause bursting.
- KEEP AWAY FROM CHILDREN.

Do not use

- On polished wood, leather, rayon fabric, or acrylic plastics.

When using this product keep out of eyes, ears, and mouth. In case of contact with eyes, rinse eyes thoroughly with water.
Stop use and ask a doctor if irritation or rash occurs. These may be signs of a serious condition.
Keep out of reach of children. If swallowed, get medical help or contact a Poison Control Center right away.

STOP USE

FIRST AID: If in eyes, hold eyes open and rinse eye slowly and gently with water for 15-20 minutes. If irritation continues, call a poison control center or doctor for advice.

Keep out of reach of children. If swallowed, get medical help or contact a Poison Control Center right away.

Directions

Hold container upright 6"-12" from surface. To clean surface, spray for 3-4 seconds until covered with mist, allow to air dry for 10 minutes. For surfaces working with food, spray for 3-4 seconds until covered with mist, allow to air dry for 10 minutes, then rinse thoroughly.

Other information

- Exposure to temperature above 130℉ may cause bursting.

Inactive ingredients

Water, Fragrance.

Package Label - Principal Display Panel

500 mL NDC: 81276-509-01